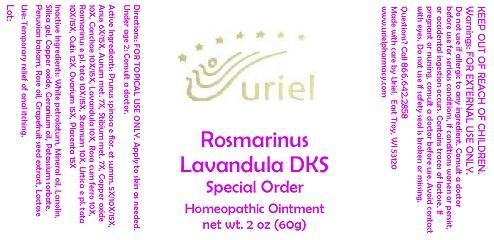 DRUG LABEL: Rosmarinus Lavandula DKS Special Order
NDC: 48951-8304 | Form: OINTMENT
Manufacturer: Uriel Pharmacy Inc.
Category: homeopathic | Type: HUMAN OTC DRUG LABEL
Date: 20150310

ACTIVE INGREDIENTS: SLOE 5 [hp_X]/1 g; BEEF 6 [hp_X]/1 g; GOLD 7 [hp_X]/1 g; ANTIMONY 7 [hp_X]/1 g; CUPRIC CATION 10 [hp_X]/1 g; OSTREA EDULIS SHELL 10 [hp_X]/1 g; LAVANDULA ANGUSTIFOLIA FLOWER 10 [hp_X]/1 g; SEDUM ROSEUM WHOLE 10 [hp_X]/1 g; IRON 10 [hp_X]/1 g; ROSMARINUS OFFICINALIS FLOWERING TOP 10 [hp_X]/1 g; TIN 10 [hp_X]/1 g; URTICA DIOICA 10 [hp_X]/1 g; SUS SCROFA SKIN 12 [hp_X]/1 g; BOS TAURUS OVARY 15 [hp_X]/1 g; BOS TAURUS PLACENTA 15 [hp_X]/1 g
INACTIVE INGREDIENTS: PETROLATUM; MINERAL OIL; LANOLIN; SILICON DIOXIDE; CUPRIC OXIDE; GERANIUM OIL, ALGERIAN TYPE; POTASSIUM SORBATE; BALSAM PERU; ROSE OIL; CITRUS PARADISI SEED; LACTOSE

Rosmarinus Lavandula DKS Special Order

INDICATIONS AND USAGE

Directions: FOR TOPICAL USE ONLY.

DOSAGE AND ADMINISTRATION

Apply to skin as needed. Under age 2: Consult a doctor.

ACTIVE INGREDIENT

Active Ingredients: Prunus spinosa e flor. et summ. 5X/10X/15X, Anus 6X/15X, Aurum met. 7X, Stibium met. 7X, Copper oxide
10X, Conchae 10X/15X, Lavandula 10X, Rosa cum ferro 10X, Rosmarinus e pl. tota 10X/15X, Stannum 10X, Urtica e pl. tota 10X/15X, Cutis 12X, Ovarium 15X, Placenta 15X

INACTIVE INGREDIENT

Inactive Ingredients: White petrolatum, Mineral oil, Lanolin, Silica gel, Copper oxide, Geranium oil, Potassium sorbate, Peruvian balsam, Rose oil, Grapefruit seed extract, Lactose

PURPOSE

Use: Temporary relief of anal itching.

KEEP OUT OF REACH OF CHILDREN.

Warnings: FOR EXTERNAL USE ONLY.
Do not use if allergic to any ingredient. Consult a doctor before use for serious conditions, if conditions worsen or persist, or accidental ingestion occurs. Contains traces of lactose. If pregnant or nursing, consult a doctor before use. Avoid contact with eyes. Do not use if safety seal is broken or missing.

QUESTIONS

Questions? Call 866.642.2858 Made with care by Uriel, East Troy, WI 53120 www.urielpharmacy.com